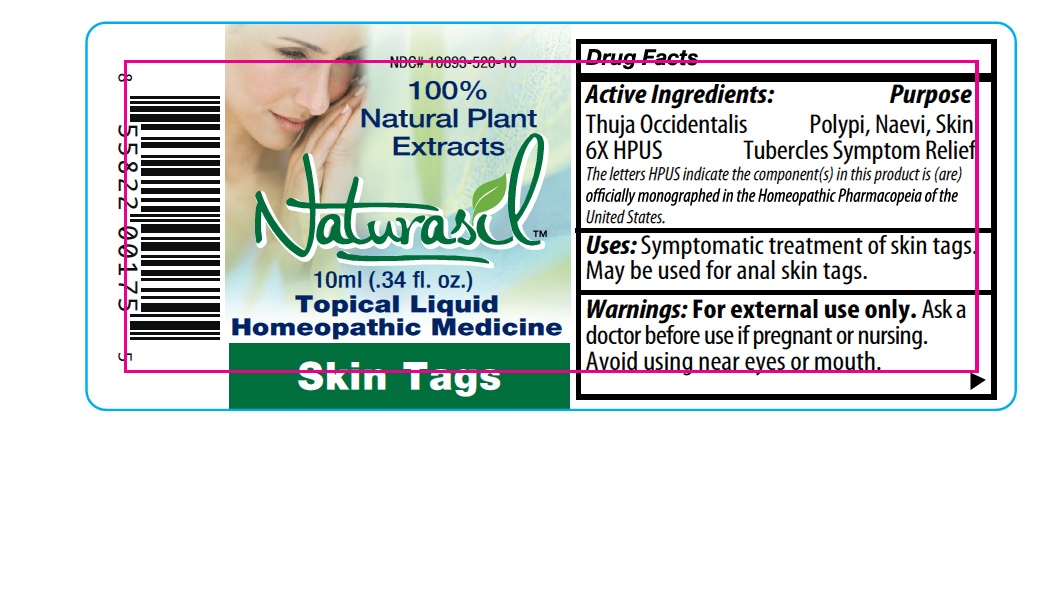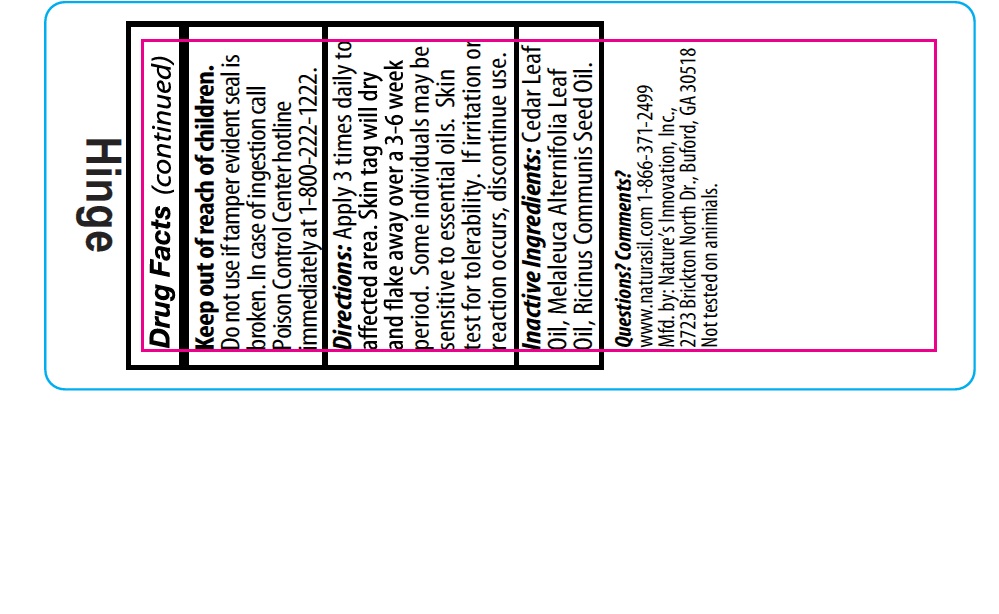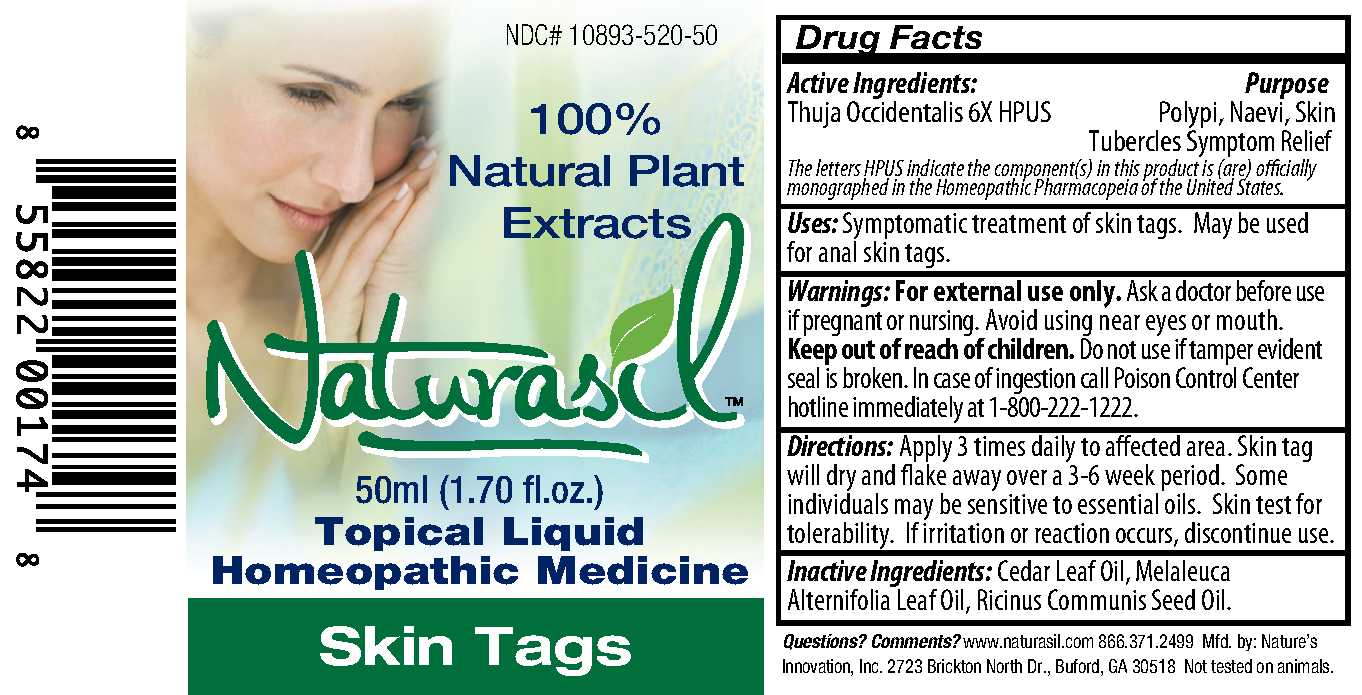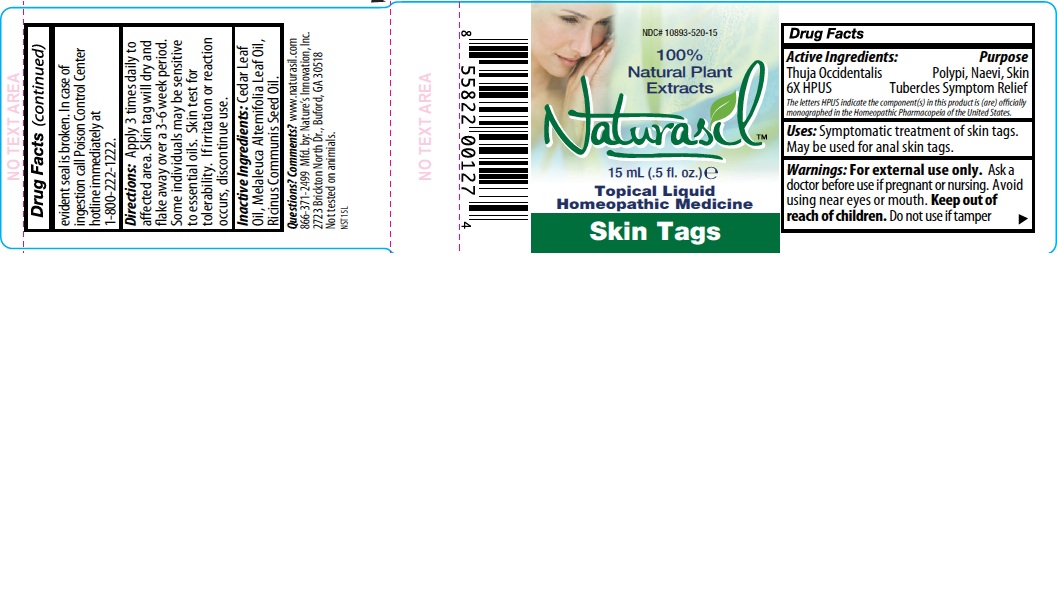 DRUG LABEL: Naturasil
NDC: 10893-520 | Form: LIQUID
Manufacturer: Nature's Innovation, Inc. 
Category: homeopathic | Type: HUMAN OTC DRUG LABEL
Date: 20250725

ACTIVE INGREDIENTS: THUJA OCCIDENTALIS LEAFY TWIG 6 [hp_X]/1 1
INACTIVE INGREDIENTS: CEDAR LEAF OIL; TEA TREE OIL; CASTOR OIL

Naturasil Skin Tags Label

Drug Facts
Active Ingredients:
Thuja Occidentalis 6X HPUS

DESCRIPTION

The letters HPUS indicate the component(s) in this product is (are) officially monographed in the Homeopathic Pharmacopeia of the United States.

Purpose

Polypi, Naevi, Skin Tubercles Symptom Relief

INDICATIONS AND USAGE

Uses: Symptomatic treatment of skin tags. May be used for anal skin tags.

Warnings: For external use only.

Ask a doctor before use if pregnant or nursing.

OTHER SAFETY INFORMATION

Avoid using near eyes or mouth.

Keep out of reach of children.

Do not use if tamper evident seal is broken.

OTHER SAFETY INFORMATION

In case of ingestion call Poison Control Center hotline immediately at 1-800-222-1222.

DOSAGE AND ADMINISTRATION

Directions: Apply 3 times daily to affected area. Skin tag will dry and flake away over a 3-6 week period. Some individuals may be sensitive to essential oils. Skin test for tolerability. If irritation or reaction occurs, discontinue use.

INACTIVE INGREDIENT

Inactive Ingredients: Cedar Leaf Oil, Melaleuca Alternifolia Leaf Oil, Ricinus Communis Seed Oil.

Questions? Comments?

www.naturasil.com 1-866-371-2499

Mfd. by: Nature's Innovation, Inc.,

2723 Brickton north Dr., Buford, GA 30518

Not tested on animals.

PACKAGE LABEL

NDC# 10893-520-

100%

Natural Plant

Extracts

Naturasil
_ml (_ fl. oz.)
Topical Liquid
Homeopathic Medicine
Skin Tags